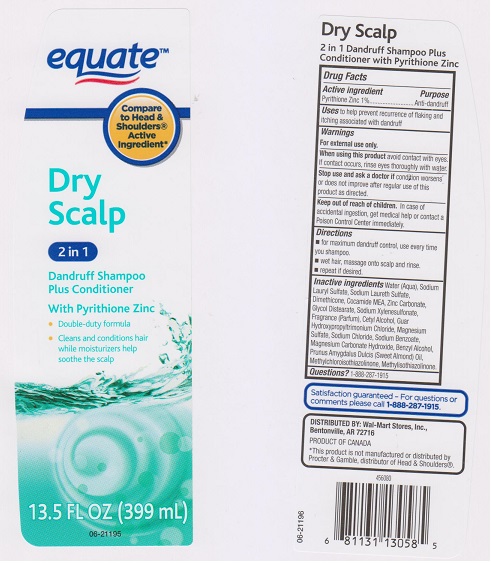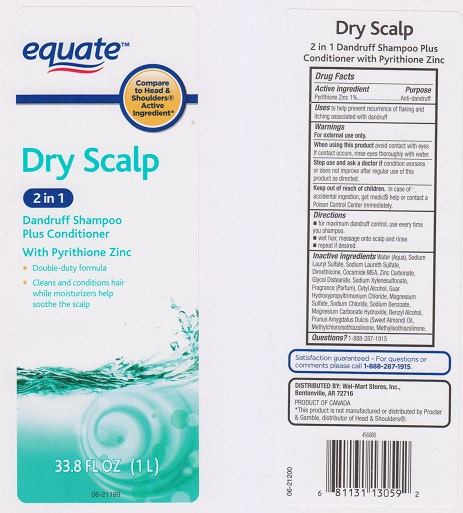 DRUG LABEL: EQUATE DRY SCALP 2 IN 1 DANDRUFF
NDC: 49035-425 | Form: SHAMPOO
Manufacturer: WAL-MART STORE INC
Category: otc | Type: HUMAN OTC DRUG LABEL
Date: 20160712

ACTIVE INGREDIENTS: PYRITHIONE ZINC 10 mg/1 mL
INACTIVE INGREDIENTS: WATER; SODIUM LAURYL SULFATE; SODIUM LAURETH-3 SULFATE; DIMETHICONE; COCO MONOETHANOLAMIDE; ZINC CARBONATE; GLYCOL DISTEARATE; SODIUM XYLENESULFONATE; CETYL ALCOHOL; GUAR HYDROXYPROPYLTRIMONIUM CHLORIDE (1.7 SUBSTITUENTS PER SACCHARIDE); MAGNESIUM SULFATE; SODIUM CHLORIDE; SODIUM BENZOATE; MAGNESIUM CARBONATE HYDROXIDE; BENZYL ALCOHOL; ALMOND OIL; METHYLCHLOROISOTHIAZOLINONE; METHYLISOTHIAZOLINONE

DRUG FACTS

Active ingredient

Pyrithione Zinc 1%

Purpose

Anti-dandruff

Uses

to help prevent recurrence of flaking and itching assocated with dandruff

Warnings

For external use only.

When using this product

avoid contact with eyes. If contact occurs, rinse eyes thoroughly with water.

Stop use and ask a doctor if

condition worsens or does not improve after regular use of this product as directed.

Keep out of reach of children.

In case of accidental ingestion, get medical help or contact a Poison Control Center immediately.

Directions

- for maximum dandruff control, use every time you shampoo.
- wet hair, massage onto scalp and rinse.
- repeat if desired.

Inactive ingredients

Water (Aqua), Sodium Lauryl Sulfate, Sodium Laureth Sulfate, Dimethicone, Cocamide MEA, Zinc Carbonate, Glycol Distearate, Sodium Xylenesulfonate, Fragrance (Parfum), Cetyl Alcohol, Guar Hydroxypropyltrimonium Chloride, Magnesium Sulfate, Sodium Chloride, Sodium Benzoate, Magnesium Carbonate Hydroxide, Benzyl Alcohol, Prunus Amygdalus Dulcis (Sweet Almond) Oil, Methylchloroisothiazolinone, Methylisothiazolinone.

Questions?

1-888-287-1915